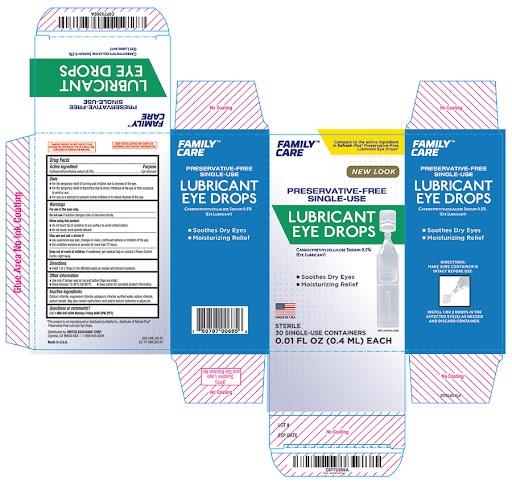 DRUG LABEL: Family Care Single Use Lubricant Eye Drop 0.4mL 30ct
NDC: 65923-576 | Form: SOLUTION/ DROPS
Manufacturer: United Exchange Corp
Category: otc | Type: HUMAN OTC DRUG LABEL
Date: 20260116

ACTIVE INGREDIENTS: CARBOXYMETHYLCELLULOSE SODIUM, UNSPECIFIED FORM 5 mg/1 mL
INACTIVE INGREDIENTS: WATER; SODIUM LACTATE; CALCIUM CHLORIDE; MAGNESIUM CHLORIDE; HYDROCHLORIC ACID; SODIUM CHLORIDE; POTASSIUM CHLORIDE; SODIUM HYDROXIDE

Family Care 685 Single Use Lubricant Eye Drop 0.4mL 30ct

Active ingredient Purpose
Carboxymethylcellulose sodium (0.5%).................................................................Eye lubricant

Uses
 For the temporary relief of burning and irritation due to dryness of the eye.
 For the temporary relief of discomfort due to minor irritations of the eye or from exposure
to wind or sun.
 For use as a lubricant to prevent further irritation or to relieve dryness of the eye.

Warnings
For use in the eyes only.

Do not use if solution changes color or becomes cloudy.

When using this product
 do not touch tip of container to any surface to avoid contamination.
 do not reuse; once opened discard.

Stop use and ask a doctor if
 you experience eye pain, changes in vision, continued redness or irritation of the eye.
 the condition worsens or persists for more than 72 hours.

Keep out of reach of children. If swallowed, get medical help or contact a Poison Control
Center right away.

Directions
 Instill 1 or 2 drops in the affected eye(s) as needed and discard container.

Other information
 Use only if tamper seal on top and bottom flaps are intact.
 Store between 15-30°C (59-86°F).  Keep carton for complete product information.

Inactive ingredients
Calcium chloride, magnesium chloride, potassium chloride, purified water, sodium chloride,
sodium lactate. May also contain hydrochloric acid and/or sodium hydroxide to adjust pH.

Questions or comments?
Call 1-888-645-8204 Monday-Friday 9AM-5PM (PST)

Distributed by: UNITED EXCHANGE CORP.
Cypress, CA 90630 USA | 1-888-645-8204
Made in U.S.A.